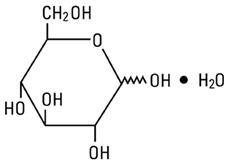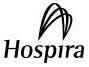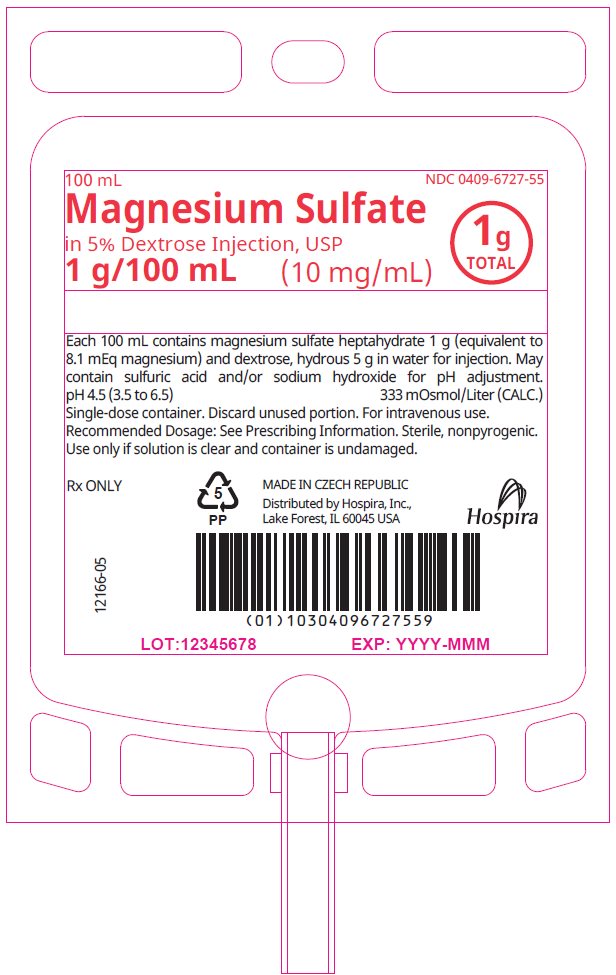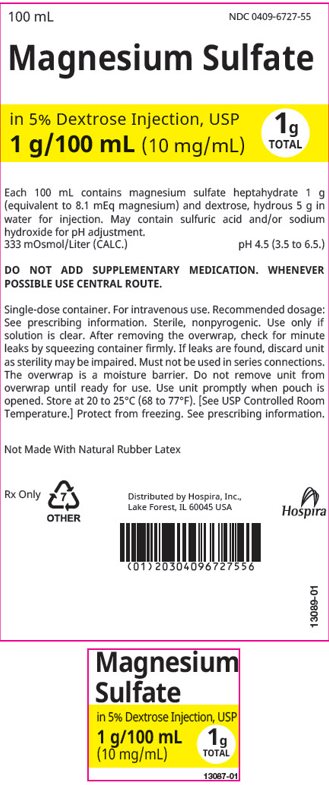 DRUG LABEL: Magnesium Sulfate in Dextrose
NDC: 0409-6727 | Form: INJECTION, SOLUTION
Manufacturer: Hospira, Inc.
Category: prescription | Type: HUMAN PRESCRIPTION DRUG LABEL
Date: 20260211

ACTIVE INGREDIENTS: MAGNESIUM SULFATE HEPTAHYDRATE 10 mg/1 mL
INACTIVE INGREDIENTS: SULFURIC ACID; SODIUM HYDROXIDE; DEXTROSE MONOHYDRATE; WATER

HIGHLIGHTS OF PRESCRIBING INFORMATION

These highlights do not include all the information needed to use MAGNESIUM SULFATE IN 5% DEXTROSE INJECTION safely and effectively. See full prescribing information for MAGNESIUM SULFATE IN 5% DEXTROSE INJECTION.
MAGNESIUM SULFATE IN DEXTROSE injection, for intravenous use
Initial U.S. Approval: 1941

1 INDICATIONS AND USAGE

Magnesium Sulfate in 5% Dextrose Injection is indicated for (1):

- Prevention of eclampsia in patients with preeclampsia (1)
- Treatment of seizures and prevention of recurrent seizures in patients with eclampsia (1)

2 DOSAGE AND ADMINISTRATION

- Administer via intravenous infusion pump (2.1)
- Recommended loading dosage is 4 to 6 grams over 15 minutes followed by a recommended maintenance dosage of 1 to 2 grams every hour; maximum recommended dosage is 30 to 40 grams over 24 hours (2.2)
- Obtain serum magnesium concentrations and assess clinical status to adjust the dose (2.2)
- Administration beyond 5 to 7 days is not recommended (2.2, 5.1)
- In patients with severe renal impairment and/or urine output less than 0.5 mL/kg/hour, administer a 4 gram loading dose followed by a maintenance dosage of 1 gram every hour; do not exceed the maximum recommended dosage of 20 grams over 48 hours (2.3)
- Do not administer Magnesium Sulfate in 5% Dextrose Injection with incompatible drugs through the same intravenous line, specifically with salicylates and alkali carbonates (2.4)

3 DOSAGE FORMS AND STRENGTHS

Supplied in premixed single-dose flexible plastic containers: (3)

- 0.01 grams/mL (1%) in 100 mL flexible plastic container containing 1 gram of magnesium sulfate in 5% dextrose injection

4 CONTRAINDICATIONS

- Heart block or myocardial damage (4)
- Diabetic coma (4)
- Myasthenia gravis (4, 5.6)

5 WARNINGS AND PRECAUTIONS

- Fetal-neonatal toxicity with prolonged use: Administration beyond 5 to 7 days is not recommended and can lead to hypocalcemia and bone abnormalities (2.2, 5.1)
- Risk of magnesium toxicity: Monitor magnesium concentrations and clinical signs of magnesium toxicity including respiratory depression, an injectable calcium salt should be immediately available to counteract hazards, for significant toxicity stop Magnesium Sulfate in 5% Dextrose Injection (5.2)
- Risk of elevated blood glucose: Solutions containing dextrose should be used with caution in patients with known prediabetes or diabetes mellitus (5.3)
- Co-administration with unapproved tocolytics: Do not use concomitantly with beta adrenergic agents such as terbutaline and calcium channel blockers such as nifedipine (5.4)
- Aluminum toxicity: Aluminum may reach toxic concentrations with prolonged parenteral administration in patients with renal impairment (5.5)
- Exacerbation of Myasthenia Gravis: Use is contraindicated because use in patients with underlying myasthenia gravis can precipitate a myasthenic crisis (5.6)

6 ADVERSE REACTIONS

The most common adverse reactions are flushing, sweating, hypotension, depressed reflexes, flaccid paralysis, hypothermia, circulatory collapse, cardiac and central nervous system (CNS) depression proceeding to respiratory paralysis and hypocalcemia. Bradycardia, pulmonary edema, decreased respiratory rate, lethargy, sedation, somnolence, visual disturbances, and hypermagnesemia are also reported (6)
To report SUSPECTED ADVERSE REACTIONS, contact Pfizer Inc., at 1-800-438-1985 or FDA at 1-800-FDA-1088 or www.fda.gov/medwatch.

7 DRUG INTERACTIONS

- Neuromuscular blocking agents: Potentiation and prolongation of neuromuscular blockade is possible with the concomitant use of Magnesium Sulfate in 5% Dextrose Injection (7)
- Narcotics and/or propofol: Potentiation and prolongation of analgesia and CNS depression is possible with the concomitant use of Magnesium Sulfate in 5% Dextrose Injection (7)
- Dihydropyridine calcium channel blockers: An exaggerated hypotensive response is possible with the concomitant use of Magnesium Sulfate in 5% Dextrose Injection (7)
- Drugs that may induce magnesium loss with concomitant use of Magnesium Sulfate in 5% Dextrose Injection: Alcohol, aminoglycosides, amphotericin B, cisplatin, cyclosporine, digitalis, loop diuretics, and thiazide diuretics (7)

8 USE IN SPECIFIC POPULATIONS

Patients with severe renal impairment and/or a urine output less than 100 mL every 4 hours are at greater risk for increased magnesium concentrations that may lead to toxicity (8.6)

FULL PRESCRIBING INFORMATION

1 INDICATIONS AND USAGE

Magnesium Sulfate in 5% Dextrose Injection is indicated for:

- Prevention of eclampsia in patients with preeclampsia
- Treatment of seizures and prevention of recurrent seizures in patients with eclampsia

2 DOSAGE AND ADMINISTRATION

2.1 Important Administration Instructions

Magnesium Sulfate in 5% Dextrose Injection is:

- A clear solution. Visually inspect Magnesium Sulfate in 5% Dextrose Injection for particulate matter and discoloration prior to administration. Do not administer unless solution is clear and colorless to slightly yellow.
- For intravenous use only
- Administered via intravenous infusion pump

Magnesium Sulfate in 5% Dextrose Injection does not require dilution prior to intravenous administration.

After removing the overwrap, check for minute leaks by squeezing the container fully. Do not administer Magnesium Sulfate in 5% Dextrose Injection if there is a leak or there is greater than 2 mL of water in the overwrap [see Description (11)].

Do not administer Magnesium Sulfate in 5% Dextrose Injection with incompatible drugs through the same intravenous line [see Dosage and Administration (2.4)]. Do not use Magnesium Sulfate in 5% Dextrose Injection in series connections.

2.2 Recommended Dosage

- The recommended loading dosage of Magnesium Sulfate in 5% Dextrose Injection in patients with eclampsia or preeclampsia is 4 to 6 grams over 15 minutes followed by a recommended maintenance dosage of 1 to 2 grams every hour.
- Obtain serum magnesium concentrations and assess clinical status to adjust the dosage.
- In patients with eclampsia, consider targeting the maintenance dosage to achieve serum magnesium concentrations of 3 to 6 mg per 100 mL (2.5 to 5 mEq per liter). For patients with recurrent eclampsia, consider giving an additional 2 gram intravenous bolus.
- For patients with eclampsia, therapy should continue until seizures cease.
- The maximum recommended dosage is 30 to 40 grams of magnesium sulfate over 24 hours.
- Administration of Magnesium Sulfate in 5% Dextrose Injection beyond 5 to 7 days is not recommended [see Warnings and Precautions (5.1)].

2.3 Dosage in Patients with Severe Renal Impairment and/or Oliguria

- In patients with severe renal impairment and/or a urine output less than 0.5 mL/kg/hour, initiate Magnesium Sulfate in 5% Dextrose Injection with a 4 gram loading dose followed by a maintenance dosage of 1 gram every hour.
- Titrate the magnesium sulfate maintenance dosage to maintain concentrations in the target range through frequent monitoring of magnesium concentrations and observation for clinical signs of magnesium toxicity (e.g., facial edema, diminished strength of deep tendon reflexes, respiratory depression). A lower maintenance dosage requirement is likely in these patients.
- Do not exceed the maximum recommended dosage of 20 grams of Magnesium Sulfate in 5% Dextrose Injection over 48 hours.

2.4 Drug Incompatibilities

Magnesium Sulfate in 5% Dextrose Injection is not compatible with administration of a variety of solutions and forms precipitates of magnesium salts. Before using Magnesium Sulfate in 5% Dextrose Injection with another parenteral product, investigate potential incompatibilities. Incompatible products that should not be coadministered include salicylates and alkali carbonates.

3 DOSAGE FORMS AND STRENGTHS

Magnesium Sulfate in 5% Dextrose Injection, USP is a clear and colorless to slightly yellow solution supplied in single-dose flexible plastic containers:

- 0.01 grams per mL (1%):
  - 100 mL flexible plastic container containing 1 gram of magnesium sulfate in 5% dextrose injection

Each 100 mL contains 5 grams of hydrous dextrose in Water for Injection.

4 CONTRAINDICATIONS

Magnesium Sulfate in 5% Dextrose Injection is contraindicated in patients:

- with heart block or myocardial damage
- in diabetic coma
- with myasthenia gravis [see Warnings and Precautions (5.6)]

5 WARNINGS AND PRECAUTIONS

5.1 Fetal-Neonatal Toxicity with Prolonged Use

Continuous administration of magnesium sulfate beyond 5 to 7 days in pregnant women can lead to hypocalcemia and bone abnormalities in the developing fetus, including skeletal demineralization and osteopenia. In addition, cases of neonatal fracture have been reported.

Neonates of women receiving Magnesium Sulfate in 5% Dextrose Injection (especially with prolonged maternal use) are at risk for magnesium toxicity including hyporeflexia, hypotonia, and respiratory depression. There is one reported case of neonatal death as the result of magnesium toxicity after transplacental exposure.

The shortest duration of magnesium sulfate treatment that can lead to fetal harm is not known. Administration of Magnesium Sulfate in 5% Dextrose Injection beyond 5 to 7 days is not recommended.

5.2 Risk of Magnesium Toxicity

Patients receiving Magnesium Sulfate in 5% Dextrose Injection are at risk for magnesium toxicity including respiratory depression, acute renal failure and rarely, pulmonary edema.

Monitor clinical signs of magnesium toxicity (for example, facial edema, diminished strength of deep tendon reflexes, respiratory depression) and magnesium concentrations during infusions of Magnesium Sulfate in 5% Dextrose Injection. Clinical indications of a safe dosage regimen include the presence of the patellar reflex (knee jerk) and absence of respiratory depression (approximately 16 breaths or more per minute). Serum magnesium concentrations usually sufficient to control convulsions range from 3 to 6 mg per 100 mL (2.5 to 5 mEq per liter). The strength of the deep tendon reflexes begins to diminish when serum magnesium concentrations exceed 4 mEq per liter. Reflexes may be absent at concentration of 10 mEq per liter, at which point respiratory paralysis is a potential hazard. An injectable calcium salt should be immediately available to counteract the potential hazards of magnesium toxicity in patients with preeclampsia and eclampsia. If there is significant magnesium toxicity, stop the Magnesium Sulfate in 5% Dextrose Injection infusion and recheck serum magnesium concentration.

Patients with renal impairment are at greater risk of magnesium toxicity because magnesium is excreted by the body solely by the kidneys [see Use in Specific Populations (8.6)]. Urine output should be maintained at a level of 100 mL per 4 hours. Monitoring serum magnesium levels and the patient's clinical status is essential to avoid the consequences of overdosage in patients with preeclampsia. Discontinuation of the magnesium infusion is recommended when urine output is less than 100 mL every 4 hours to avoid magnesium toxicity, especially if serum creatinine is increasing progressively.

5.3 Risk of Elevated Blood Glucose

Solutions containing dextrose should be used with caution in patients with known prediabetes or diabetes mellitus given the risk of elevated blood glucose.

5.4 Co-administration with Unapproved Tocolytics

Do not use Magnesium Sulfate in 5% Dextrose Injection with unapproved tocolytics (e.g., beta adrenergic agents such as terbutaline, or with calcium channel blockers such as nifedipine). Serious adverse events including pulmonary edema and hypotension have occurred [see Drug Interactions (7)].

5.5 Aluminum Toxicity

Magnesium Sulfate in 5% Dextrose Injection contains aluminum that may be toxic (Magnesium Sulfate in 5% Dextrose Injection contains less than 25 mcg/L of aluminum). Aluminum may reach toxic concentrations with prolonged parenteral administration in patients with renal impairment.

Patients with renal impairment who receive parenteral concentrations of aluminum at greater than 4 to 5 mcg/kg/day, accumulate aluminum at concentrations associated with central nervous system and bone toxicity. Tissue loading may occur at even lower rates of administration.

5.6 Exacerbation of Myasthenia Gravis

Magnesium Sulfate in 5% Dextrose Injection is contraindicated in patients with known myasthenia gravis.

Use of magnesium sulfate in patients with underlying myasthenia gravis can precipitate a myasthenic crisis. Myasthenic crisis is a life-threatening condition characterized by neuromuscular respiratory failure. Symptoms of myasthenic crisis may include difficulty swallowing, ptosis, facial droop, weakness and/or difficulty breathing that may require intubation.

If myasthenic crisis is suspected, discontinue use of Magnesium Sulfate in 5% Dextrose Injection immediately. Secure the patient's airway. Consider intensive care unit admission and elective intubation, if respiratory failure is anticipated. Once the airway is secure, confirm the diagnosis. Therapies include plasmapheresis and plasma exchange or intravenous immunoglobulin (IVIG) and immunomodulating therapy in addition to high-dose glucocorticoids.

6 ADVERSE REACTIONS

The following adverse reactions have been identified in clinical studies or postmarketing reports. Because these reactions are reported voluntarily from a population of uncertain size, it is not always possible to reliably estimate their frequency or establish a causal relationship to drug exposure.

Cardiovascular: | hypotension, circulatory collapse, cardiac depression including bradycardia
Central Nervous System: | central nervous system depression leading to respiratory paralysis, visual disturbances, flushing, sweating, hypothermia
Metabolic: | hypocalcemia with signs of tetany, hypermagnesemia
Neurologic: | lethargy, sedation, somnolence, myasthenic crisis
Neuromuscular: | depressed deep tendon reflexes, flaccid paralysis
Pulmonary: | decreased respiratory rate, pulmonary edema

7 DRUG INTERACTIONS

Table 1 presents the potential clinical impact of medications that may be commonly administered concomitantly with Magnesium Sulfate in 5% Dextrose Injection in the clinical setting.

Table 1: Potential Clinically Significant Drug Interactions with Magnesium Sulfate in 5% Dextrose Injection [For drug incompatibility information [see Dosage and Administration (2.4)].]
Neuromuscular Blocking Agents
Clinical Impact: | - Potentiation and prolongation of neuromuscular blockade is possible with the concomitant use of magnesium sulfate and neuromuscular blocking agents [see Clinical Pharmacology (12.2)]. - The underlying mechanism of this interaction may involve suppression of peripheral neuromuscular function by decreasing acetylcholine release, reduction of endplate sensitivity, and decreased muscle fiber excitability with magnesium sulfate therapy.
Intervention: | - Monitor respiration and the depth of neuromuscular blockade frequently (e.g., train-of-four monitoring) when a neuromuscular blocking agent is used concomitantly with Magnesium Sulfate in 5% Dextrose Injection. - Adjust the dosage of the neuromuscular blocking agent accordingly to maintain the desired level of musculoskeletal activity. The amount of reversal agent(s) required to achieve adequate reversal of the neuromuscular blocking agent(s) may also be increased.
Examples: | - Depolarizing neuromuscular blockers: succinylcholine - Non-depolarizing neuromuscular blockers: atracurium, cisatracurium, pancuronium, rocuronium, vecuronium
Narcotics and/or Propofol
Clinical Impact: | - Potentiation and prolongation of analgesia and CNS depression is possible with the concomitant use of Magnesium Sulfate in 5% Dextrose Injection with narcotics and/or propofol. The potential for magnesium sulfate to affect other CNS depressants is unknown [see Clinical Pharmacology (12.2)]. - The underlying mechanism of this interaction may involve antagonism of N-methyl-D-aspartate (NMDA) by magnesium sulfate therapy.
Intervention: | - Monitor the depth of CNS depression frequently using a reliable instrument. - Adjust the narcotic and/or propofol dosage accordingly to maintain the desired level of analgesia and sedation.
Examples: | - Narcotics and propofol
Dihydropyridine Calcium Channel Blockers
Clinical Impact: | - An exaggerated hypotensive response is possible with the concomitant use of Magnesium Sulfate in 5% Dextrose Injection with dihydropyridine calcium channel blockers. The potential for magnesium sulfate to affect other calcium channel blockers (e.g., diltiazem and verapamil) is unknown [see Clinical Pharmacology (12.2)].
Intervention: | - Monitor vital signs (heart rate, blood pressure, respiration) frequently. - Supportive care and/or discontinuation of the calcium channel blocker may be required.
Examples: | - Amlodipine, clevidipine, felodipine, isradipine, nicardipine, nifedipine, nimodipine, and nisoldipine
Drugs that May Induce Magnesium Loss
Clinical Impact: | - Reduced magnesium concentrations may impact efficacy
Intervention: | - Monitor magnesium concentrations frequently and adjust the Magnesium Sulfate in 5% Dextrose Injection dosage to maintain concentrations in the target range [see Dosage and Administration (2)].
Examples: | - Alcohol, aminoglycosides, amphotericin B, cisplatin, cyclosporine, digitalis, loop diuretics, thiazide diuretics

8 USE IN SPECIFIC POPULATIONS

8.1 Pregnancy

Risk Summary

Magnesium Sulfate in 5% Dextrose Injection is indicated in pregnant women for the prevention of eclampsia in women with preeclampsia and the treatment of seizures and prevention of recurrent seizures in women with eclampsia. Fetal, neonatal, and maternal risks are discussed throughout the labeling.

Clinical Considerations

Labor or Delivery:

Magnesium Sulfate in 5% Dextrose Injection is not approved for the treatment of pre-term labor.

Administration of Magnesium Sulfate in 5% Dextrose Injection to pregnant women longer than 5 to 7 days may lead to hypocalcemia and bone abnormalities in the developing fetus, including skeletal demineralization and osteopenia [see Warnings and Precautions (5.1)].

8.2 Lactation

The use of intravenous magnesium in pregnant women increases human milk magnesium concentrations only slightly and oral absorption of magnesium by the infant is poor. The effect of intravenous magnesium on milk production is unknown. The developmental and health benefits to the neonate of breastfeeding should be considered along with the mother's clinical need for Magnesium Sulfate in 5% Dextrose Injection and any potential adverse effects on the breastfed infant from Magnesium Sulfate in 5% Dextrose Injection or from the underlying maternal condition.

8.4 Pediatric Use

The safety and effectiveness of Magnesium Sulfate in 5% Dextrose Injection have been established for the prevention of eclampsia in adolescents with preeclampsia and the treatment of seizures and prevention of recurrent seizures in adolescents with eclampsia. Dosing recommendation in pregnant adolescent patients are the same as for pregnant adult patients [see Dosage and Administration (2.2)].

8.6 Renal Impairment

Magnesium is excreted solely by the kidneys. Patients with severe renal impairment (urine output less than 100 mL per 4 hours) are at greater risk for increased magnesium concentrations that may lead to magnesium toxicity [see Warnings and Precautions (5.2) and Clinical Pharmacology (12.3)]. In patients with severe renal impairment, dosage reduction is recommended and the maximum recommended dosage is lower than patients with normal renal function [see Dosage and Administration (2.3)].

10 OVERDOSAGE

Manifestations of magnesium toxicity include a drop in blood pressure, difficulty breathing, and disappearance of the patellar reflex. As serum magnesium rises above 4 mEq per liter, the deep tendon reflexes decrease. As the serum magnesium level approaches 10 mEq per liter, the tendon reflexes disappear and respiratory paralysis may occur [see Warnings and Precautions (5.2)]. Other signs and symptoms of magnesium overdosage include flushing, sweating, hypotension, weakness, hypothermia, circulatory collapse, cardiac and central nervous system depression proceeding to respiratory paralysis, cardiac arrest, and prolongation of PR and QRS intervals. Patients with renal impairment and underlying neuromuscular diseases such as myasthenia gravis may experience magnesium intoxication at lower magnesium concentrations (Magnesium Sulfate in 5% Dextrose Injection is contraindicated in patients with myasthenia gravis).

If patient is experiencing magnesium toxicity, immediately discontinue Magnesium Sulfate in 5% Dextrose Injection. Artificial respiration may be required. Administer an injectable calcium salt to counteract the potential hazards of magnesium toxicity [see Warnings and Precautions (5.2)].

Hypermagnesemia in the newborn (after administration of Magnesium Sulfate in 5% Dextrose Injection to the mother) may require resuscitation and assisted ventilation via endotracheal intubation or intermittent positive pressure ventilation as well as intravenous calcium.

11 DESCRIPTION

Magnesium Sulfate in 5% Dextrose Injection, USP is a sterile, nonpyrogenic solution of magnesium sulfate heptahydrate and dextrose in water for injection for intravenous use. Each 100 mL contains 1 gram of magnesium sulfate heptahydrate and dextrose, hydrous 5 grams in water for injection [see How Supplied/Storage and Handling (16)]. Magnesium Sulfate in 5% Dextrose Injection, USP may contain sulfuric acid and/or sodium hydroxide for pH adjustment. The pH is 4.5 (3.5 to 6.5).

Magnesium Sulfate, USP heptahydrate is chemically known as sulfuric acid magnesium salt (1:1), heptahydrate and chemically designated MgSO4 ∙ 7H2O, with a molecular weight of 246.47. It occurs as colorless crystals or white powder freely soluble in water.

Dextrose, USP is chemically designated D-glucose, monohydrate, a hexose sugar freely soluble in water. The molecular formula is C6H12O6 ∙ H2O and the molecular weight is 198.17. It has the following structural formula:

Water for Injection, USP is chemically designated H2O.

Water can permeate from inside the flexible plastic container into the overwrap [see Dosage and Administration (2.1)] but not in amounts sufficient to affect the solution significantly. Solutions in contact with the plastic container may leach out certain chemical components from the plastic in very small amounts; however, biological testing was supportive of the safety of the plastic container materials. Exposure to temperatures above 25°C (77°F) during transport and storage will lead to minor losses in moisture content. Higher temperatures lead to greater losses. It is unlikely that these minor losses will lead to clinically significant changes within the expiration period.

12 CLINICAL PHARMACOLOGY

12.1 Mechanism of Action

Magnesium prevents seizures in patients with preeclampsia and controls seizures in patients with eclampsia by blocking neuromuscular transmission and decreasing the amount of acetylcholine liberated at the end plate by the motor nerve impulse. Magnesium has a depressant effect on the central nervous system [see Drug Interactions (7)]. Magnesium acts peripherally to produce vasodilation.

12.2 Pharmacodynamics

With intravenous administration of magnesium sulfate the onset of anticonvulsant action is immediate and lasts about 30 minutes. The estimated magnesium concentration (above baseline) required to elicit half-maximum effect (EC50) on systolic and diastolic blood pressure in pregnant women with preeclampsia that received intravenous magnesium sulfate therapy was reported to be 1.5 and 1.8 mEq per liter (1.9 and 2.2 mg per dL), respectively, in a published study. Effective anticonvulsant serum concentrations range from 2.5 to 7.5 mEq per liter.

Drug Interaction Studies

The following information is based upon published case reports and clinical studies that could not be confirmed by an adequately controlled study, but still warrant consideration given the potential risks involved [see Drug Interactions (7)].

Neuromuscular Blocking Agents:

Potentiation and prolongation of neuromuscular blockade requiring modification of the neuromuscular blocking agent dosage and/or increased reversal agent requirements were reported in preeclamptic women who received magnesium sulfate treatment who underwent subsequent surgery (for example, caesarian section) with anesthesia that included either a depolarizing (d-tubocurarine, succinylcholine) or nondepolarizing neuromuscular blocking agent (vecuronium, rocuronium).

Narcotics and/or Propofol:

Potentiation and prolongation of analgesic and/or sedative effects as well as a reduced requirement for an intravenous narcotic (fentanyl, sufentanil, tramadol), intrathecal narcotic (fentanyl), and/or intravenous propofol was reported in magnesium sulfate treated patients who required surgery or intensive care that also included narcotic and/or propofol therapy.

Dihydropyridine Calcium Channel Blockers:

An exaggerated hypotensive response (blood pressure 80–93/49–60 mm Hg) was reported in preeclamptic women who received oral nifedipine in addition to magnesium sulfate treatment. Blood pressure returned to previous levels within approximately 30 minutes with supportive care.

12.3 Pharmacokinetics

Distribution

Approximately 1 to 2% of total body magnesium is located in the extracellular fluid space. Magnesium is 30% bound to albumin.

Elimination

The average half-life and systemic clearance of magnesium sulfate in preeclamptic women is approximately 4 to 5 hours and 4 to 5 liters per hour, respectively.

Excretion:

Magnesium is excreted solely by the kidney at a rate proportional to the serum concentration and glomerular filtration.

Specific Populations

Patients with Renal Impairment:

Plasma magnesium concentrations of 7 to 12.3 mEq per liter (8.6 to 15.1 mg per dL) were reported in preeclamptic women with a urine output less than 100 mL per 4 hours that received 20 grams of magnesium sulfate intravenously over 2 to 8 hours in a published study [see Dosage and Administration (2.3) and Use in Specific Populations (8.6)].

13 NONCLINICAL TOXICOLOGY

13.1 Carcinogenesis, Mutagenesis, Impairment of Fertility

Studies with Magnesium Sulfate in 5% Dextrose Injection have not been performed to evaluate carcinogenic potential, mutagenic potential or effects on fertility.

16 HOW SUPPLIED/STORAGE AND HANDLING

Magnesium Sulfate in 5% Dextrose Injection, USP is a clear solution supplied in single-dose flexible plastic containers (see Table 2).

Table 2: How Supplied Information
NDC Number (Unit of Sale) | Concentration | Total Magnesium Sulfate [As the heptahydrate;] | Total Magnesium Ion | Magnesium Sulfate Concentration | Magnesium Ion Concentration | Osmolarity [Osmolarity was calculated.]
NDC 0409-6727-23 Case of 24 single-dose flexible plastic containers | 1 g/100 mL (10 mg/mL) | 1 g | 8.1 mEq | 0.01 g/mL (1%) | 8.1 mEq/100 mL | 333 mOsmol/liter
NDC 0409-6727-50 Case of 50 single-dose flexible plastic containers | 1 g/100 mL (10 mg/mL) | 1 g | 8.1 mEq | 0.01 g/mL (1%) | 8.1 mEq/100 mL | 333 mOsmol/liter

Storage

Store at 20°C to 25°C (68°F to 77°F). [See USP Controlled Room Temperature.]

Protect from freezing.

17 PATIENT COUNSELING INFORMATION

Magnesium Sulfate in 5% Dextrose Injection is typically administered to pregnancy women in emergent situations. When feasible, advise the patient and family of the following:

Fetal-Neonatal Toxicity Reported With Prolonged Use

Continuous administration of Magnesium Sulfate in 5% Dextrose Injection in pregnant women beyond 5 to 7 days can lead to hypocalcemia and bone abnormalities in the developing fetus, including skeletal demineralization and osteopenia. In addition, cases of neonatal fracture have been reported [see Warnings and Precautions (5.1)].

Risk of Magnesium Toxicity

Pregnant women receiving Magnesium Sulfate in 5% Dextrose Injection are at risk for magnesium toxicity, including facial edema, diminished strength of deep tendon reflexes, and respiratory depression [see Warnings and Precautions (5.2)].

Distributed by Hospira, Inc., Lake Forest, IL 60045 USA

LAB-1086-5.0

PRINCIPAL DISPLAY PANEL - 100 mL Bag Label

100 mL
NDC 0409-6727-55

Magnesium Sulfate
in 5% Dextrose Injection, USP

1 g/100 mL

(10 mg/mL)

1g
TOTAL

Each 100 mL contains magnesium sulfate heptahydrate 1 g (equivalent to
8.1 mEq magnesium) and dextrose, hydrous 5 g in water for injection. May
contain sulfuric acid and/or sodium hydroxide for pH adjustment.

pH 4.5 (3.5 to 6.5)
333 mOsmol/Liter (CALC.)

Single-dose container. Discard unused portion. For intravenous use.
Recommended Dosage: See Prescribing Information. Sterile, nonpyrogenic.
Use only if solution is clear and container is undamaged.

Rx ONLY

12166-05

5
PP

MADE IN CZECH REPUBLIC

Distributed by Hospira, Inc.,
Lake Forest, IL 60045 USA

Hospira

LOT:12345678

EXP: YYYY-MMM

PRINCIPAL DISPLAY PANEL - 100 mL Bag Overwrap

100 mL
NDC 0409-6727-55

Magnesium Sulfate

in 5% Dextrose Injection, USP
1 g/100 mL (10 mg/mL)

1g
TOTAL

Each 100 mL contains magnesium sulfate heptahydrate 1 g
(equivalent to 8.1 mEq magnesium) and dextrose, hydrous 5 g in
water for injection. May contain sulfuric acid and/or sodium
hydroxide for pH adjustment.

333 mOsmol/Liter (CALC.)
pH 4.5 (3.5 to 6.5.)

DO NOT ADD SUPPLEMENTARY MEDICATION. WHENEVER
POSSIBLE USE CENTRAL ROUTE.

Single-dose container. For intravenous use. Recommended dosage:
See prescribing information. Sterile, nonpyrogenic. Use only if
solution is clear. After removing the overwrap, check for minute
leaks by squeezing container firmly. If leaks are found, discard unit
as sterility may be impaired. Must not be used in series connections.
The overwrap is a moisture barrier. Do not remove unit from
overwrap until ready for use. Use unit promptly when pouch is
opened. Store at 20 to 25°C (68 to 77°F). [See USP Controlled Room
Temperature.] Protect from freezing. See prescribing information.

Not Made With Natural Rubber Latex

Rx Only

7
OTHER

Distributed by Hospira, Inc.,
Lake Forest, IL 60045 USA

Hospira

13089-01